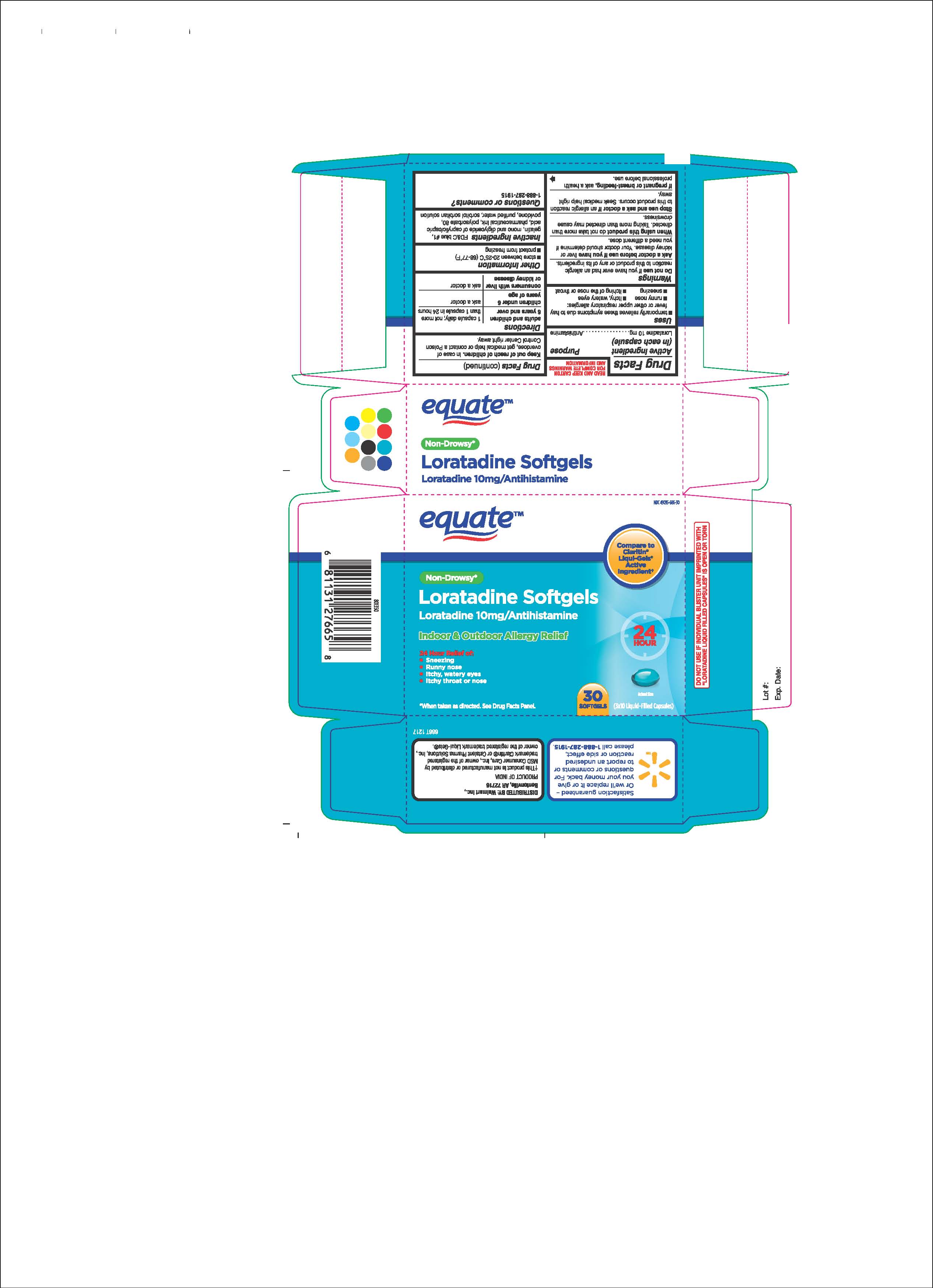 DRUG LABEL: LORATADINE SOFTGELS
NDC: 49035-686 | Form: CAPSULE, LIQUID FILLED
Manufacturer: Wal-Mart Stores Inc
Category: otc | Type: HUMAN OTC DRUG LABEL
Date: 20180516

ACTIVE INGREDIENTS: LORATADINE 10 mg/1 1
INACTIVE INGREDIENTS: WATER; FD&C BLUE NO. 1; GELATIN; SORBITOL; GLYCERYL CAPRYLOCAPRATE; POLYSORBATE 80; POVIDONES

WALMART 686T

Active ingredient(in each capsule)

Loratadine 10 mg

Purpose

Antihistamine

Uses

temporarily relieves these symptoms due to hay fever or other upper respiratory allergies:

- runny nose
- itchy, watery eyes
- sneezing
- itching of the nose or throat

Warnings

DO NOT USE IF YOU HAVE EVER HAD AN ALLERGIC REACTION TO THIS PRODUCT OR ANY OF ITS INGREDIENTS.

WHEN USING THIS PRODUCT DO NOT TAKE MORE THAN DIRECTED. TAKING MORE THAN DIRECTED MAY CAUSE DROWSINESS.

STOP USE AND ASK A DOCTOR IF AN ALLERGIC REACTION TO THIS PRODUCT OCCURS. SEEK MEDICAL HELP RIGHT AWAY.

IF PREGNANT OR BREASTFEEDING, ASK A HEALTH PROFESSIONAL BEFORE USE.

Do not use if you have ever had an allergic reaction to this product or any of its ingredients.

Ask a doctor before use if you have liver or kidney disease. Your doctor should determine if you need a different dose.

When using this product do not take more than directed. Taking more than directed may cause drowsiness.

Stop use and ask a doctor if

- an allergic reaction to this product occurs. Seek medical help right away.
- side effects occur.

PREGNANCY OR BREAST FEEDING

If pregnant or breast-feeding, ask a health care professional before use.

Keep out of reach of children. In case of overdose, get medical help or contact a Poison Control Center right away.

Directions

ADULTS AND CHILDREN 6 YEARS AND OVER: 1 CAPSULE DAILY; NOT MORE THAN 1 CAPSULE IN 24 HOURS.

CHILDREN UNDER 6 YEARS OF AGE: ASK A DOCTOR.

CONSUMERS WITH LIVER OR KIDNEY DISEASE: ASK A DOCTOR.

Other information

STORE BETWEEN 20-25 DEGREES CELSIUS (67-77 DEGREES FAHRENHEIT)

PROTECT FROM FREEZING

Inactive ingredients

FD&C BLUE #1, GELATIN, MONO AND DIGLYCERIDE OF CAPRYLIC/CAPRIC ACID, PHARMACEUTICAL INK, POLYSORBATE 80, POVIDONE, PURIFIED WATER, SORBITOL SORBITAN SOLUTION.